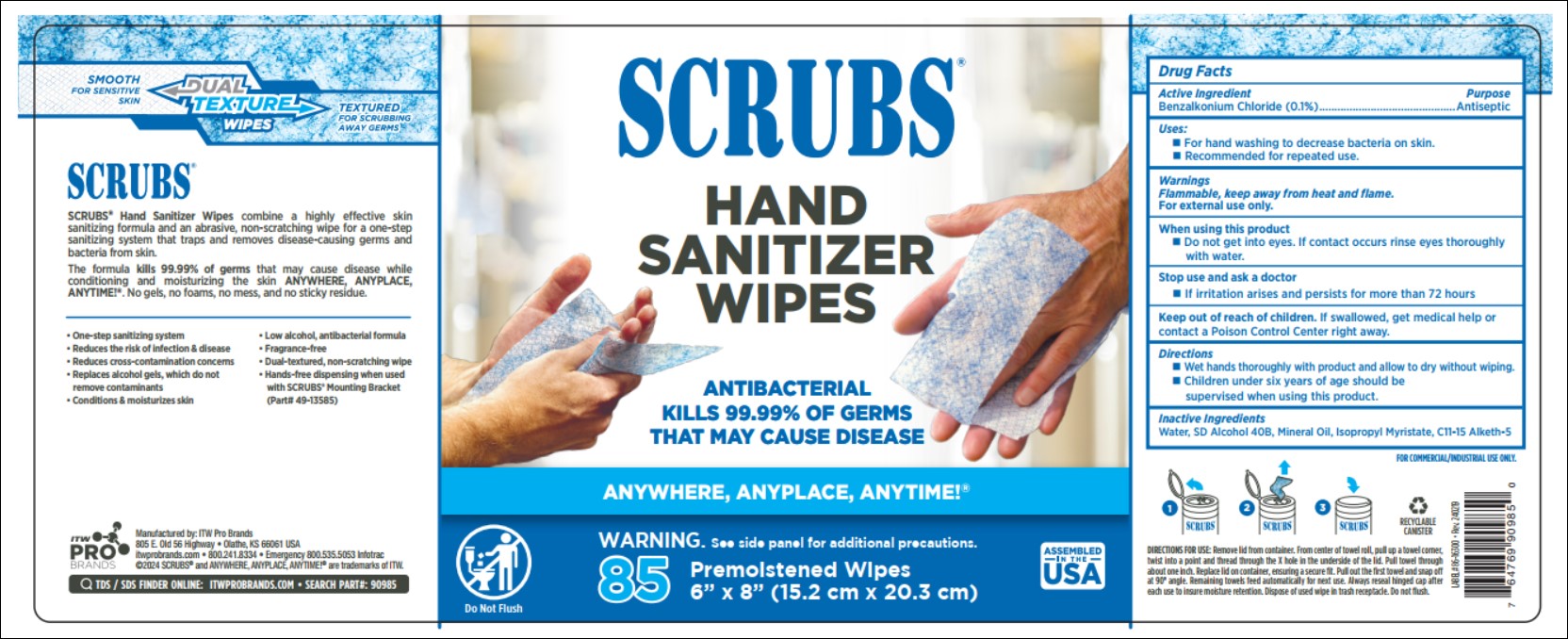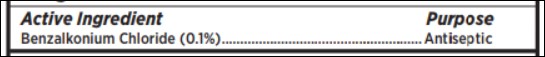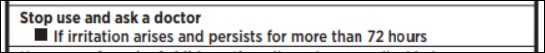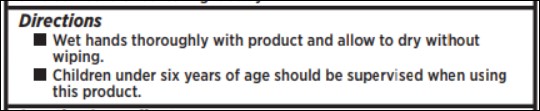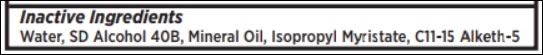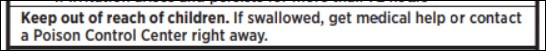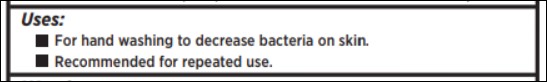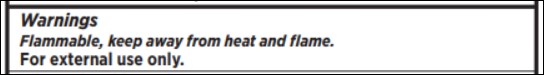 DRUG LABEL: SCRUBS Hand Sanitizer Wipes
NDC: 51239-2909 | Form: CLOTH
Manufacturer: ITW Pro Brands
Category: otc | Type: HUMAN OTC DRUG LABEL
Date: 20240222

ACTIVE INGREDIENTS: BENZALKONIUM CHLORIDE 0.1 g/100 g
INACTIVE INGREDIENTS: MINERAL OIL; ISOPROPYL MYRISTATE; ALCOHOL; WATER; C11-15 PARETH-5

SCRUBS Hand Sanitizer Wipes